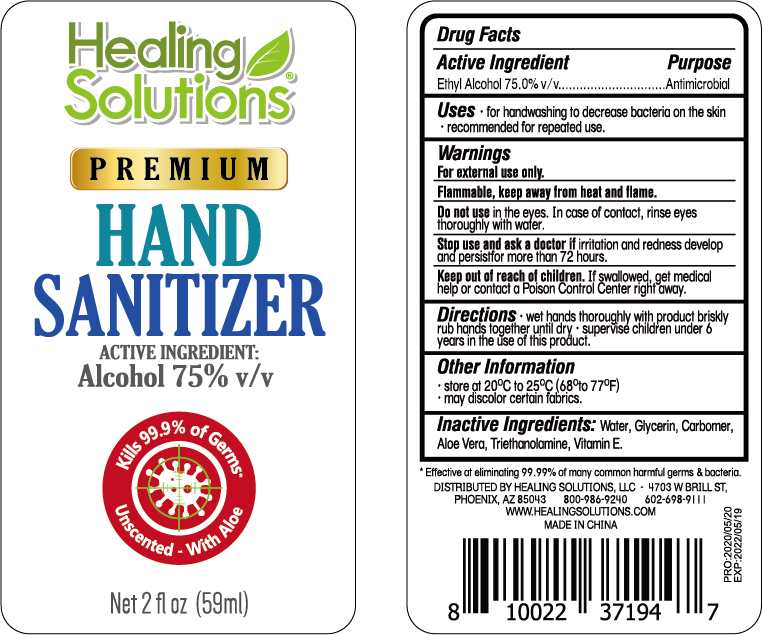 DRUG LABEL: Healing Solutions Premium Hand Sanitizer
NDC: 75112-004 | Form: SOLUTION
Manufacturer: Zhejiang Shenying Technology Co., Ltd. Jiaojiang Branch
Category: otc | Type: HUMAN OTC DRUG LABEL
Date: 20200608

ACTIVE INGREDIENTS: ALCOHOL 75 mL/100 mL
INACTIVE INGREDIENTS: GLYCERIN; WATER; CARBOMER 934; ALPHA-TOCOPHEROL ACETATE; TROLAMINE; ALOE VERA WHOLE

NA

Active Ingredient(s)

Ethyl Alcohol 75%

Purpose

Antimicrobial

Use

For hand washing to decrease bacteria on the skin

Recommended for repeated use

Warnings

For external use only

Flammable. Keep away from heat and flame

When using this product do not use in the eyes. In case of contact, rinse eyes thoroughly with water.

Stop use and ask a doctor if irritation and redness develop and persist for more than 72 hours

Keep out of reach of children. If swallowed, get medical help or contact a Poison Control Center right away.

Directions

Wet hands thoroughly with product.

Rub hands together briskly untill dry

Supervise children under 6 years in the use of this product

Other information

Store at 20-25C (68-77F)

May discolor certain fabrics

Inactive ingredients

Water, glycerin, carbomer, aloe vera, triethanolamine, tocopheryl acetate